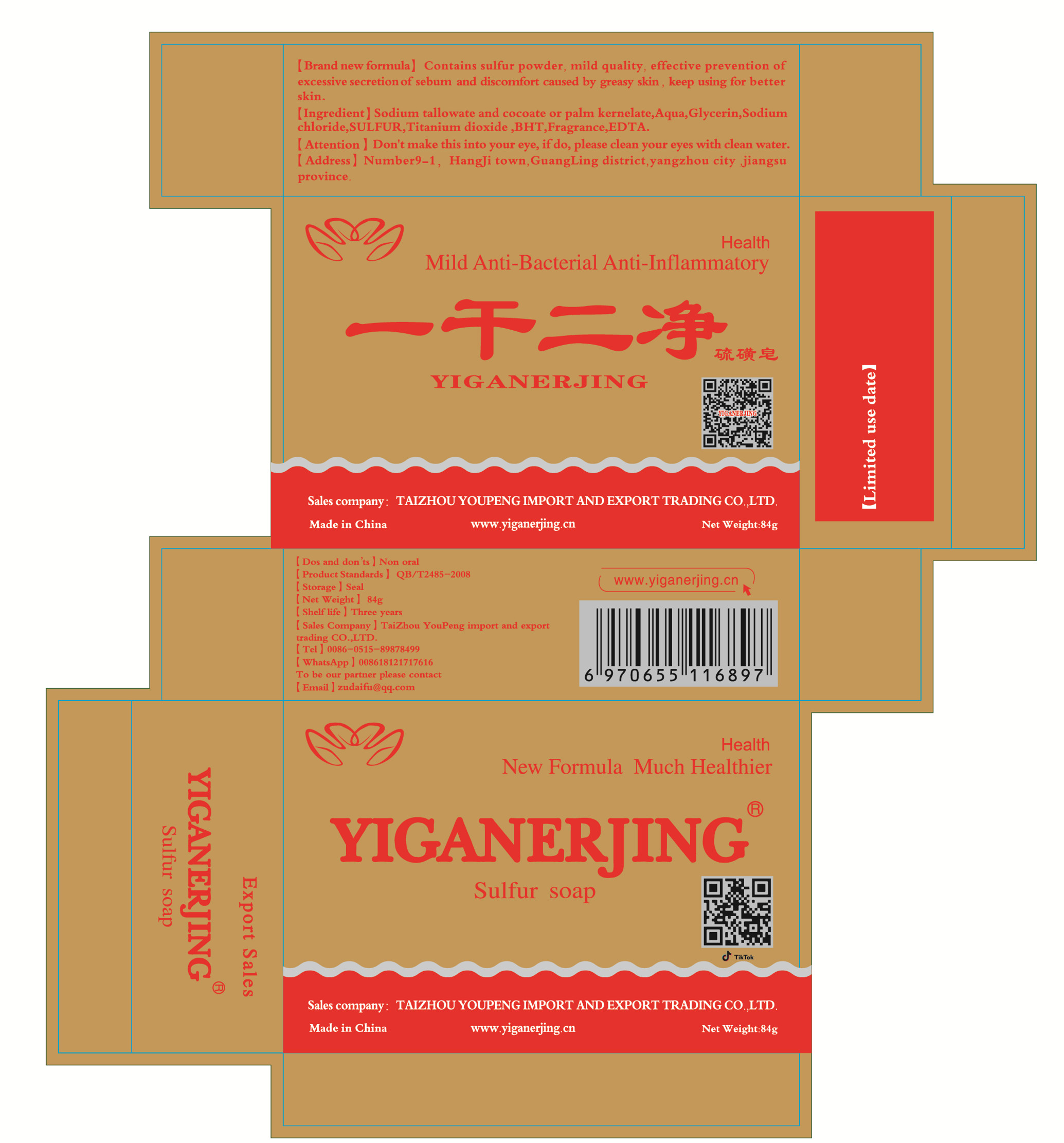 DRUG LABEL: YIGANERJING  SuifurSoap
NDC: 71939-003 | Form: SOAP
Manufacturer: TAIZHOU YOUPENG IMPORT AND EXPORT TRADING CO.,LTD.
Category: otc | Type: HUMAN OTC DRUG LABEL
Date: 20220310

ACTIVE INGREDIENTS: TITANIUM DIOXIDE 0.168 g/84 g; EDETIC ACID 0.0672 g/84 g; SULFUR 0.84 g/84 g
INACTIVE INGREDIENTS: SODIUM CHLORIDE; FRAGRANCE LAVENDER & CHIA F-153480; GLYCERIN; BUTYLATED HYDROXYTOLUENE; WATER

DOSAGE AND ADMINISTRATION

Store in a cool and dry place

INACTIVE INGREDIENT

Aque,Glycerin,Sodium chloride,BHT,Fragrance

INDICATIONS AND USAGE

When using sulfur soap to clean the face, first rub the sulfur soap in the palm of the hand until it foams, then rub the face, this can reduce the irritation of the sulfur component on the skin.

ACTIVE INGREDIENT

sulfur

Titanium dioxide

EDTA

keep out of reach of children

PURPOSE

Disinfection
Sterilization

WARNINGS

Although the concentration of sulfur soap is lower than that of clinically used sulfur suppositories, it is still not recommended for long-term continuous use. It can be used indirectly once a day or once every three days.